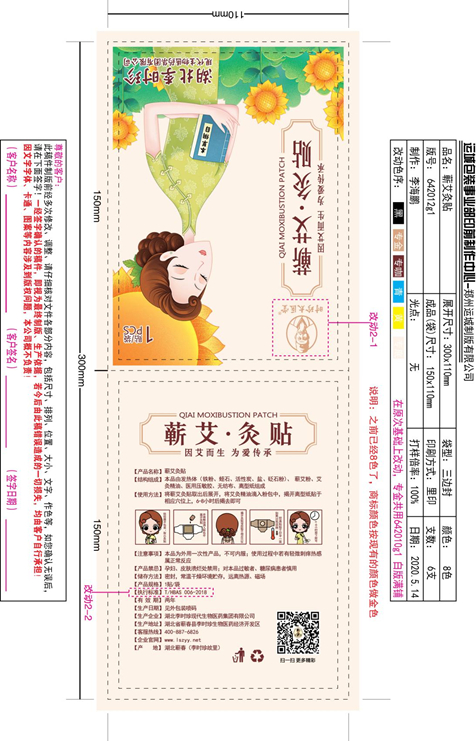 DRUG LABEL: Chinese medicine patch
NDC: 72624-001 | Form: TAPE
Manufacturer: Hubei Lishizhen Modern Biological Medicine Group Co.,Ltd.
Category: otc | Type: HUMAN OTC DRUG LABEL
Date: 20201231

ACTIVE INGREDIENTS: BUTYLENE GLYCOL 48 g/240 mL
INACTIVE INGREDIENTS: WATER; HYDROXYETHYL CELLULOSE, UNSPECIFIED; POLYETHYLENE GLYCOL, UNSPECIFIED; PHENOXYETHANOL; CHLORPHENESIN

ACTIVE INGREDIENT

butylene glycol (20%): 48g/package or 48mL/package

INACTIVE INGREDIENT

water (77.52%): 186.048mL/package

hydroxyethylcellulose (1.6%): 3.84mL/package

polyethylene glycol 300000 (0.5%): 1.2mL/package

phenoxyethanol (0.3%): 0.72mL/package

chlorphenesin (0.08%): 0.192mL/package

PURPOSE

It is a heat disposable paster incorporating chemicals that provides heat therapy for body.

WHEN USING

Conditioning neck, back, hands and feet and other rheumatism pain and spleen and stomach caused by cold injury, deficiency diarrhea and other conditions.

DO NOT USE

If irritation or discomfort occurs, discontinue the use and consult a physician.

STOP USE

If irritation or discomfort occurs, discontinue the use and consult a physician.

ASK DOCTOR

If irritation or discomfort occurs, discontinue the use and consult a physician.

Ask doctor/pharmacist when you current use other drugs.

Keep out of reach of children and away from eyes and ears.

Please contact us when you have any questions.

PREGNANCY

Pregnant or breast feeding women shall follow doctor advice.

INDICATIONS AND USAGE

Pain relief, hot release, warming uterus, hemostatic, can be used to improve the conditioning neck, back, hands and feet and other rheumatism pain and spleen and stomach caused by cold injury, deficiency diarrhea and other conditions.

Apply one paster on stomach venter.

DOSAGE AND ADMINISTRATION

One time one paster.

DOSAGE FORMS AND STRENGTHS

It is a paster.

A paster one time, or reapply as needed.

The active ingredient strength is 20%.

WARNINGS

If irritation or discomfort occurs, discontinue the use and consult a physician.

Very slippery on surfaces, clean spills immediately.

Keep out of reach of children and pets.